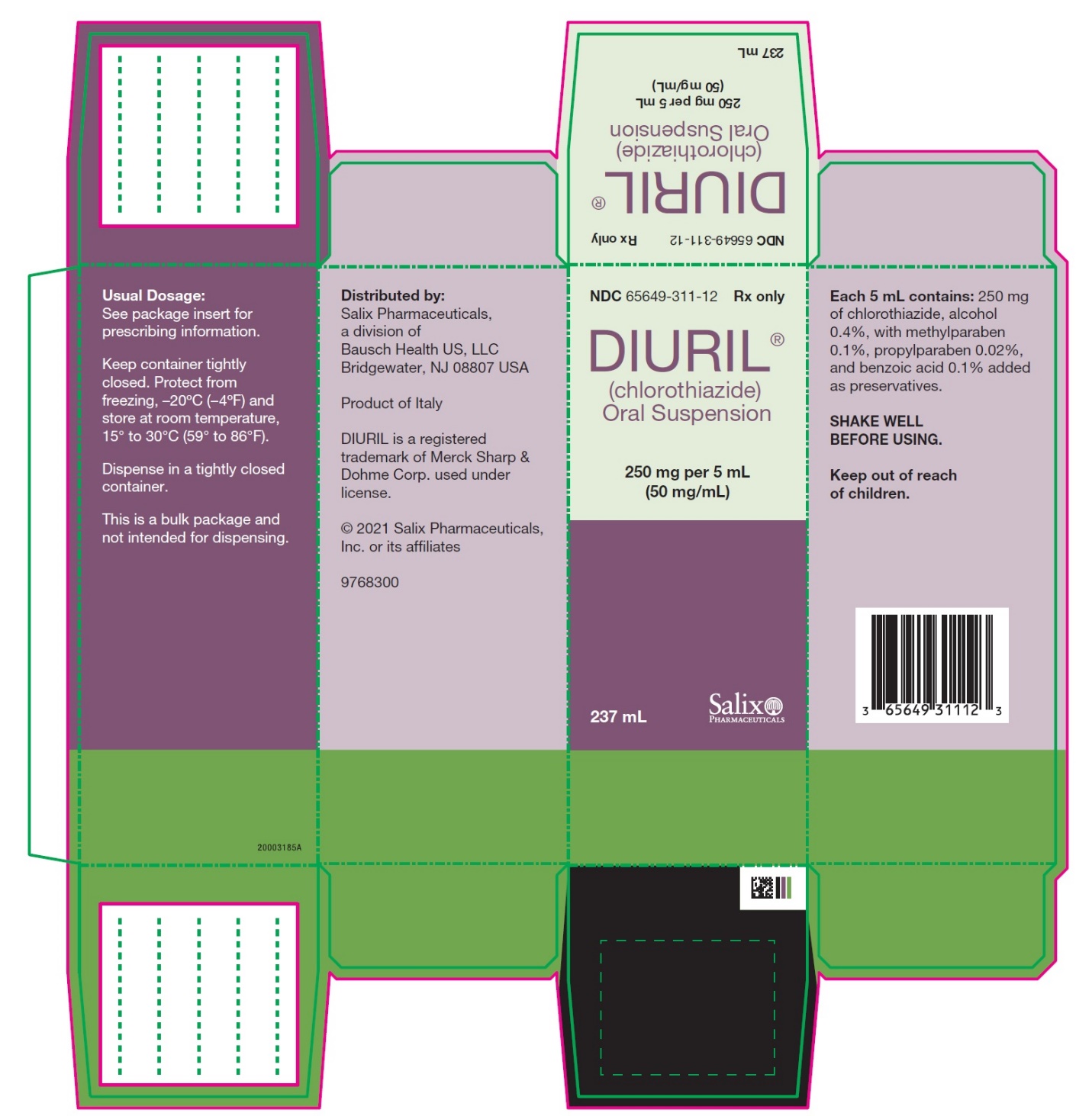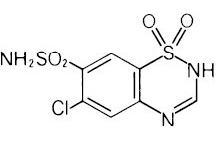 DRUG LABEL: DIURIL
NDC: 65649-311 | Form: SUSPENSION
Manufacturer: Salix Pharmaceuticals, Inc
Category: prescription | Type: HUMAN PRESCRIPTION DRUG LABEL
Date: 20211101

ACTIVE INGREDIENTS: CHLOROTHIAZIDE 250 mg/5 mL
INACTIVE INGREDIENTS: ALCOHOL; METHYLPARABEN; PROPYLPARABEN; BENZOIC ACID; D&C YELLOW NO. 10; GLYCERIN; WATER; SUCROSE; TRAGACANTH

DIURIL®
(chlorothiazide) Oral Suspension

DESCRIPTION

DIURIL® (chlorothiazide) is a diuretic and antihypertensive. It is 6-chloro-2H-1,2,4-benzothiadiazine-7-sulfonamide 1,1-dioxide. Its empirical formula is C7H6CIN3O4S2 and its structural formula is:

It is a white, or practically white, crystalline powder with a molecular weight of 295.72, which is very slightly soluble in water, but readily soluble in dilute aqueous sodium hydroxide. It is soluble in urine to the extent of about 150 mg per 100 mL at pH 7.

DIURIL Oral Suspension contains 250 mg of chlorothiazide per 5 mL, alcohol 0.4%, with methylparaben 0.1%, propylparaben 0.02%, and benzoic acid 0.1% added as preservatives. The inactive ingredients are D&C Yellow 10, flavors, glycerin, purified water, sodium saccharin, sucrose and tragacanth.

CLINICAL PHARMACOLOGY

The mechanism of the antihypertensive effect of thiazides is unknown. DIURIL does not usually affect normal blood pressure.

DIURIL affects the distal renal tubular mechanism of electrolyte reabsorption. At maximal therapeutic dosage all thiazides are approximately equal in their diuretic efficacy.

DIURIL increases excretion of sodium and chloride in approximately equivalent amounts. Natriuresis may be accompanied by some loss of potassium and bicarbonate.

After oral use diuresis begins within 2 hours, peaks in about 4 hours and lasts about 6 to 12 hours.

Pharmacokinetics and Metabolism

DIURIL is not metabolized but is eliminated rapidly by the kidney. The plasma half-life of chlorothiazide is 45-120 minutes. After oral doses, 10-15% of the dose is excreted unchanged in the urine. Chlorothiazide crosses the placental but not the blood-brain barrier and is excreted in breast milk.

INDICATIONS AND USAGE

DIURIL is indicated as adjunctive therapy in edema associated with congestive heart failure, hepatic cirrhosis, and corticosteroid and estrogen therapy.

DIURIL has also been found useful in edema due to various forms of renal dysfunction such as nephrotic syndrome, acute glomerulonephritis, and chronic renal failure.

DIURIL is indicated in the management of hypertension either as the sole therapeutic agent or to enhance the effectiveness of other antihypertensive drugs in the more severe forms of hypertension.

Use in Pregnancy - Routine use of diuretics during normal pregnancy is inappropriate and exposes mother and fetus to unnecessary hazard. Diuretics do not prevent development of toxemia of pregnancy and there is no satisfactory evidence that they are useful in the treatment of toxemia.

Edema during pregnancy may arise from pathologic causes or from the physiologic and mechanical consequences of pregnancy. Thiazides are indicated in pregnancy when edema is due to pathologic causes, just as they are in the absence of pregnancy (see PRECAUTIONS, Pregnancy). Dependent edema in pregnancy, resulting from restriction of venous return by the gravid uterus, is properly treated through elevation of the lower extremities and use of support stockings. Use of diuretics to lower intravascular volume in this instance is illogical and unnecessary. During normal pregnancy there is hypervolemia which is not harmful to the fetus or the mother in the absence of cardiovascular disease. However, it may be associated with edema, rarely generalized edema. If such edema causes discomfort, increased recumbency will often provide relief. Rarely this edema may cause extreme discomfort which is not relieved by rest. In these instances, a short course of diuretic therapy may provide relief and be appropriate.

CONTRAINDICATIONS

Anuria.

Hypersensitivity to this product or to other sulfonamide-derived drugs.

WARNINGS

Use with caution in severe renal disease. In patients with renal disease, thiazides may precipitate azotemia. Cumulative effects of the drug may develop in patients with impaired renal function.

Thiazides should be used with caution in patients with impaired hepatic function or progressive liver disease, since minor alterations of fluid and electrolyte balance may precipitate hepatic coma.

Thiazides may add to or potentiate the action of other antihypertensive drugs.

Sensitivity reactions may occur in patients with or without a history of allergy or bronchial asthma.

The possibility of exacerbation or activation of systemic lupus erythematosus has been reported.

Lithium generally should not be given with diuretics (see PRECAUTIONS, Drug Interactions).

PRECAUTIONS

General

All patients receiving diuretic therapy should be observed for evidence of fluid or electrolyte imbalance: namely, hyponatremia, hypochloremic alkalosis, and hypokalemia. Serum and urine electrolyte determinations are particularly important when the patient is vomiting excessively or receiving parenteral fluids. Warning signs or symptoms of fluid and electrolyte imbalance, irrespective of cause, include dryness of mouth, thirst, weakness, lethargy, drowsiness, restlessness, confusion, seizures, muscle pains or cramps, muscular fatigue, hypotension, oliguria, tachycardia, and gastrointestinal disturbances such as nausea and vomiting.

Hypokalemia may develop, especially with brisk diuresis, when severe cirrhosis is present or after prolonged therapy.

Interference with adequate oral electrolyte intake will also contribute to hypokalemia. Hypokalemia may cause cardiac arrhythmias and may also sensitize or exaggerate the response of the heart to the toxic effects of digitalis (e.g., increased ventricular irritability). Hypokalemia may be avoided or treated by use of potassium-sparing diuretics or potassium supplements such as foods with a high potassium content.

Although any chloride deficit is generally mild and usually does not require specific treatment except under extraordinary circumstances (as in liver disease or renal disease), chloride replacement may be required in the treatment of metabolic alkalosis.

Dilutional hyponatremia may occur in edematous patients in hot weather; appropriate therapy is water restriction, rather than administration of salt, except in rare instances when the hyponatremia is life-threatening. In actual salt depletion, appropriate replacement is the therapy of choice.

Hyperuricemia may occur or acute gout may be precipitated in certain patients receiving thiazides.

In diabetic patients dosage adjustments of insulin or oral hypoglycemic agents may be required. Hyperglycemia may occur with thiazide diuretics. Thus latent diabetes mellitus may become manifest during thiazide therapy.

The antihypertensive effects of the drug may be enhanced in the post-sympathectomy patient.

If progressive renal impairment becomes evident, consider withholding or discontinuing diuretic therapy.

Thiazides have been shown to increase the urinary excretion of magnesium; this may result in hypomagnesemia.

Thiazides may decrease urinary calcium excretion. Thiazides may cause intermittent and slight elevation of serum calcium in the absence of known disorders of calcium metabolism. Marked hypercalcemia may be evidence of hidden hyperparathyroidism. Thiazides should be discontinued before carrying out tests for parathyroid function.

Increases in cholesterol and triglyceride levels may be associated with thiazide diuretic therapy.

Laboratory Tests

Periodic determination of serum electrolytes to detect possible electrolyte imbalance should be done at appropriate intervals.

Drug Interactions

When given concurrently the following drugs may interact with thiazide diuretics.

Alcohol, Barbiturates, or Narcotics - potentiation of orthostatic hypotension may occur.

Antidiabetic Drugs (Oral Agents and Insulin) - dosage adjustment of the antidiabetic drug may be required.

Other Antihypertensive Drugs - additive effect or potentiation.

Cholestyramine and Colestipol Resins - Both cholestyramine and colestipol resins have the potential of binding thiazide diuretics and reducing diuretic absorption from the gastrointestinal tract.

Corticosteroids, ACTH - intensified electrolyte depletion, particularly hypokalemia.

Pressor Amines (e.g., Norepinephrine) - possible decreased response to pressor amines but not sufficient to preclude their use.

Skeletal Muscle Relaxants, Nondepolarizing (e.g., Tubocurarine) - possible increased responsiveness to the muscle relaxant.

Lithium - generally should not be given with diuretics. Diuretic agents reduce the renal clearance of lithium and add a high risk of lithium toxicity. Refer to the package insert for lithium preparations before use of such preparations with DIURIL.

Non-steroidal Anti-inflammatory Drugs (NSAIDs) Including Selective Cyclooxygenase-2 (COX-2) Inhibitors - In some patients, the administration of a non-steroidal anti-inflammatory agent including a selective COX-2 inhibitor can reduce the diuretic, natriuretic, and antihypertensive effects of loop, potassium-sparing and thiazide diuretics. Therefore, when DIURIL and non-steroidal anti-inflammatory agents or selective COX-2 inhibitors are used concomitantly, the patient should be observed closely to determine if the desired effect of the diuretic is obtained.

In some patients with compromised renal function (e.g., elderly patients or patients who are volume-depleted, including those on diuretic therapy) who are being treated with NSAIDs, including selective COX-2 inhibitors, the co-administration of angiotensin II receptor antagonists or ACE inhibitors may result in a further deterioration of renal function, including possible acute renal failure. These effects are usually reversible.

These interactions should be considered in patients taking NSAIDs including selective COX-2 inhibitors concomitantly with diuretics and angiotensin II antagonists or ACE inhibitors. Therefore, the combination should be administered with caution, especially in the elderly.

Drug/Laboratory Test Interactions

Thiazides should be discontinued before carrying out tests for parathyroid function (see PRECAUTIONS, General).

Carcinogenesis, Mutagenesis, Impairment of Fertility

Carcinogenicity studies have not been conducted with chlorothiazide.

Chlorothiazide was not mutagenic in vitro in the Ames microbial mutagen test (using a maximum concentration of 5 mg/plate and Salmonella typhimurium strains TA98 and TA100) and was not mutagenic and did not induce mitotic nondisjunction in diploid-strains of Aspergillus nidulans.

Chlorothiazide had no adverse effects on fertility in female rats at doses up to 60 mg/kg/day and no adverse effects on fertility in male rats at doses up to 40 mg/kg/day. These doses are 1.5 and 1 times** the recommended maximum human dose, respectively, when compared on a body weight basis.

Pregnancy

TERATOGENIC EFFECTS

Teratogenic Effects - Although reproduction studies performed with chlorothiazide doses of 50 mg/kg/day in rabbits, 60 mg/kg/day in rats and 500 mg/kg/day in mice revealed no external abnormalities of the fetus or impairment of growth and survival of the fetus due to chlorothiazide, such studies did not include complete examinations for visceral and skeletal abnormalities. It is not known whether chlorothiazide can cause fetal harm when administered to a pregnant woman; however, thiazides cross the placental barrier and appear in cord blood. DIURIL should be used during pregnancy only if clearly needed (see INDICATIONS AND USAGE).

NONTERATOGENIC EFFECTS

Nonteratogenic Effects - Chlorothiazide may cause fetal or neonatal jaundice, thrombocytopenia, and possibly other adverse reactions which have occurred in the adult.

Nursing Mothers

Because of the potential for serious adverse reactions in nursing infants from DIURIL, a decision should be made whether to discontinue nursing or to discontinue the drug, taking into account the importance of the drug to the mother.

Pediatric Use

There are no well-controlled clinical trials in pediatric patients. Information on dosing in this age group is supported by evidence from empiric use in pediatric patients and published literature regarding the treatment of hypertension in such patients (see DOSAGE AND ADMINISTRATION, Infants and Children).

_____________

**Calculations based on a human body weight of 50 kg

Geriatric Use

Clinical studies of DIURIL did not include sufficient numbers of subjects aged 65 and over to determine whether they respond differently from younger subjects. Other reported clinical experience has not identified differences in responses between the elderly and younger patients. In general, dose selection for an elderly patient should be cautious, usually starting at the low end of the dosing range, reflecting the greater frequency of decreased hepatic, renal, or cardiac function, and of concomitant disease or other drug therapy.

This drug is known to be substantially excreted by the kidney, and the risk of toxic reactions to this drug may be greater in patients with impaired renal function. Because elderly patients are more likely to have decreased renal function, care should be taken in dose selection, and it may be useful to monitor renal function (see WARNINGS).

ADVERSE REACTIONS

The following adverse reactions have been reported and, within each category, are listed in order of decreasing severity:

Body as a Whole: Weakness.

Cardiovascular: Hypotension, including orthostatic hypotension (may be aggravated by alcohol, barbiturates, narcotics or antihypertensive drugs).

Digestive: Pancreatitis, jaundice (intrahepatic cholestatic jaundice), diarrhea, vomiting, sialadenitis, cramping, constipation, gastric irritation, nausea, anorexia.

Hematologic: Aplastic anemia, agranulocytosis, leukopenia, hemolytic anemia, thrombocytopenia.

Hypersensitivity: Anaphylactic reactions, necrotizing angiitis (vasculitis and cutaneous vasculitis), respiratory distress including pneumonitis and pulmonary edema, photosensitivity, fever, urticaria, rash, purpura.

Metabolic: Electrolyte imbalance (see PRECAUTIONS), hyperglycemia, glycosuria, hyperuricemia.

Musculoskeletal: Muscle spasm.

Nervous System/Psychiatric: Vertigo, paresthesias, dizziness, headache, restlessness.

Renal: Renal failure, renal dysfunction, interstitial nephritis (see WARNINGS).

Skin: Erythema multiforme including Stevens-Johnson syndrome, exfoliative dermatitis including toxic epidermal necrolysis, alopecia.

Special Senses: Transient blurred vision, xanthopsia.

Urogenital: Impotence.

Whenever adverse reactions are moderate or severe, thiazide dosage should be reduced or therapy withdrawn.

To report SUSPECTED ADVERSE REACTIONS, contact Salix Pharmaceuticals at 1-800-321-4576 or FDA at 1-800-FDA-1088 or www.fda.gov/medwatch.

OVERDOSAGE

The most common signs and symptoms observed are those caused by electrolyte depletion (hypokalemia, hypochloremia, hyponatremia) and dehydration resulting from excessive diuresis. If digitalis has also been administered, hypokalemia may accentuate cardiac arrhythmias.

In the event of overdosage, symptomatic and supportive measures should be employed. Emesis should be induced or gastric lavage performed. Correct dehydration, electrolyte imbalance, hepatic coma and hypotension by established procedures. If required, give oxygen or artificial respiration for respiratory impairment.

The degree to which chlorothiazide sodium is removed by hemodialysis has not been established.

The oral LD50 of chlorothiazide is 8.5 g/kg, greater than 10 g/kg, and greater than 1 g/kg, in the mouse, rat and dog, respectively.

DOSAGE AND ADMINISTRATION

Therapy should be individualized according to patient response. Use the smallest dosage necessary to achieve the required response.

Adults

For Edema

The usual adult dosage is 500 mg to 1,000 mg (10 mL to 20 mL) once or twice a day. Many patients with edema respond to intermittent therapy, i.e., administration on alternate days or on three to five days each week. With an intermittent schedule, excessive response and the resulting undesirable electrolyte imbalance are less likely to occur.

For Control of Hypertension

The usual adult starting dosage is 500 mg or 1,000 mg (10 mL to 20 mL) a day as a single or divided dose. Dosage is increased or decreased according to blood pressure response. Rarely some patients may require up to 2,000 mg (40 mL) a day in divided doses.

Infants and Children

For Diuresis and For Control of Hypertension

The usual pediatric dosage is 5 mg to 10 mg per pound (10 mg/kg to 20 mg/kg) per day in single or two divided doses, not to exceed 375 mg per day (2.5 mL to 7.5 mL or ½ to 1½ teaspoonfuls of the oral suspension daily) in infants up to 2 years of age or 1,000 mg per day in children 2 to 12 years of age. In infants less than 6 months of age, doses up to 15 mg per pound (30 mg/kg) per day in two divided doses may be required (see PRECAUTIONS, Pediatric Use).

HOW SUPPLIED

DIURIL® (chlorothiazide) Oral Suspension, 250 mg of chlorothiazide per 5 mL, is a yellow, syrupy liquid, and is supplied as follows:

NDC 65649-311-12 250 mg per 5 mL 237 mL Storage

DIURIL (chlorothiazide) Oral Suspension: Keep container tightly closed. Protect from freezing, –20°C (–4°F) and store at room temperature, 15° to 30°C (59° to 86°F).

Distributed by:
Salix Pharmaceuticals,
a division of Bausch Health US, LLC
Bridgewater, NJ 08807 USA

DIURIL is a registered trademark of Merck Sharp & Dohme Corp. used under license.

© 2021 Salix Pharmaceuticals, Inc. or its affiliates

Rev. 11/2021

9768400

Package Carton- Principal Display Panel

NDC 65649-311-12

Rx only

DIURIL®

(chlorothiazide)

Oral Suspension

250 mg per 5 mL

(50 mg/mL)

237 mL

Salix

PHARMACEUTICALS